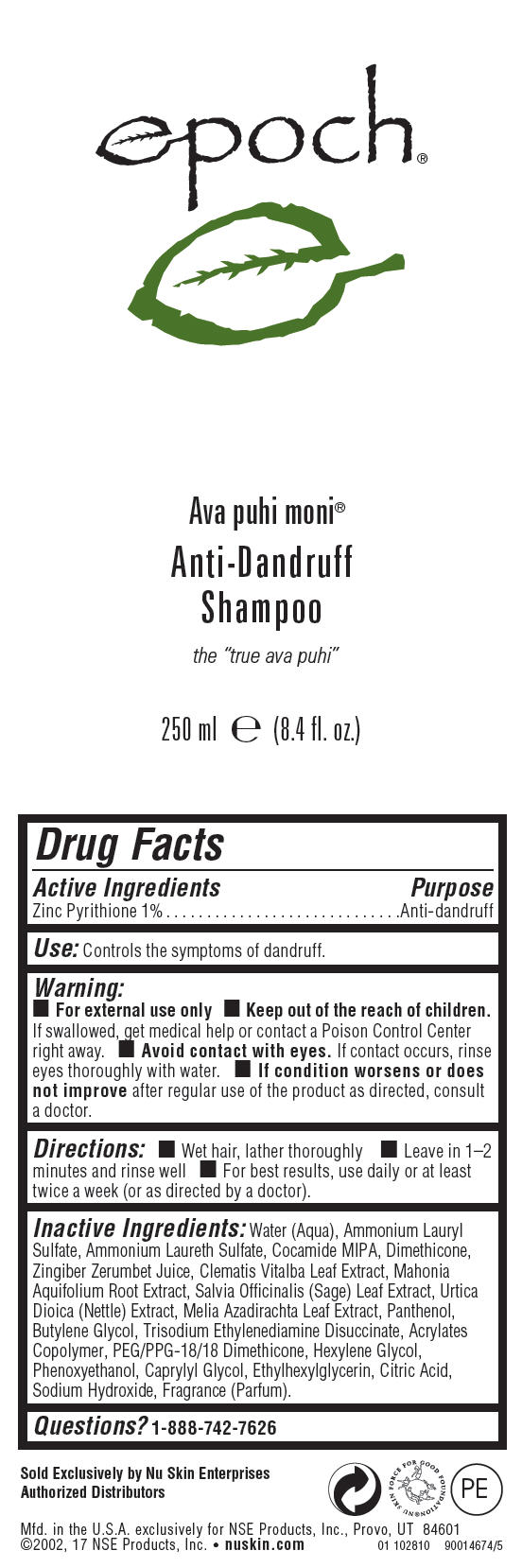 DRUG LABEL: Epoch Ava Puhi Moni Anti-Dandruff
NDC: 62839-6745 | Form: SHAMPOO
Manufacturer: NSE Products, Inc.
Category: otc | Type: HUMAN OTC DRUG LABEL
Date: 20241231

ACTIVE INGREDIENTS: PYRITHIONE ZINC 65.7 g/1000 mL
INACTIVE INGREDIENTS: WATER; Ammonium Lauryl Sulfate; COCO MONOISOPROPANOLAMIDE; Dimethicone; Phenoxyethanol; Caprylyl Glycol; Sodium Hydroxide; CITRIC ACID MONOHYDRATE; Trisodium Ethylenediamine Disuccinate; Ethylhexylglycerin; Hexylene Glycol; Panthenol; AZADIRACHTA INDICA LEAF; Butylene Glycol; BERBERIS AQUIFOLIUM ROOT; CLEMATIS VITALBA LEAF; PEG/PPG-18/18 Dimethicone; SAGE; URTICA DIOICA LEAF

Epoch® Ava Puhi Moni® Anti-Dandruff Shampoo

Drug Facts

Active Ingredients

Zinc Pyrithione 1%

Purpose

Anti-dandruff

Use

Controls the symptoms of dandruff.

Warning

- For external use only

KEEP OUT OF REACH OF CHILDREN

- Keep out of the reach of children. If swallowed, get medical help or contact a Poison Control Center right away.

- Avoid contact with eyes. If contact occurs, rinse eyes thoroughly with water.

ASK DOCTOR

- If condition worsens or does not improve after regular use of the product as directed, consult a doctor.

Directions

- Wet hair, lather thoroughly
- Leave in 1–2 minutes and rinse well
- For best results, use daily or at least twice a week (or as directed by a doctor).

Inactive Ingredients

Water (Aqua), Ammonium Lauryl Sulfate, Ammonium Laureth Sulfate, Cocamide MIPA, Dimethicone, Zingiber Zerumbet Juice, Clematis Vitalba Leaf Extract, Mahonia Aquifolium Root Extract, Salvia Officinalis (Sage) Leaf Extract, Urtica Dioica (Nettle) Extract, Melia Azadirachta Leaf Extract, Panthenol, Butylene Glycol, Trisodium Ethylenediamine Disuccinate, Acrylates Copolymer, PEG/PPG-18/18 Dimethicone, Hexylene Glycol, Phenoxyethanol, Caprylyl Glycol, Ethylhexylglycerin, Citric Acid, Sodium Hydroxide, Fragrance (Parfum).

Questions?

1-888-742-7626

PRINCIPAL DISPLAY PANEL - 250 ml Bottle Label

epoch®

Ava puhi moni®

Anti-Dandruff
Shampoo

the "true ava puhi"

250 ml e (8.4 fl. oz.)